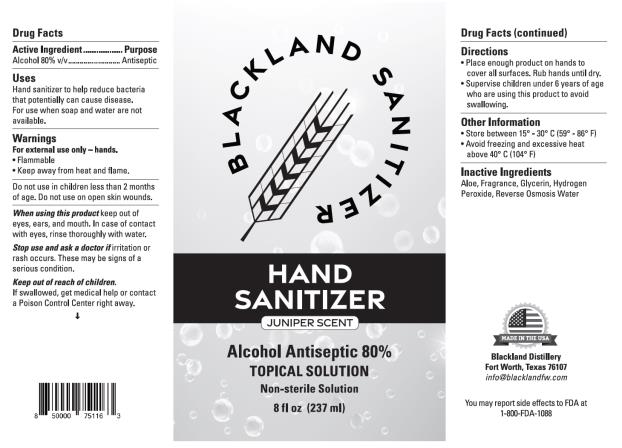 DRUG LABEL: Hand Sanitizer
NDC: 78816-001 | Form: LIQUID
Manufacturer: Blackland Distillery
Category: otc | Type: HUMAN OTC DRUG LABEL
Date: 20200616

ACTIVE INGREDIENTS: ALCOHOL 80 mL/100 mL
INACTIVE INGREDIENTS: GLYCERIN; WATER; ALOE; HYDROGEN PEROXIDE

Hand Sanitizer

Drug Facts

Purpose

Alcohol 80% v/v ……… Antiseptic

Uses

Hand sanitizer to help reduce bacteria that potentially can cause disease. For use when soap and water are not available.

Warning

For external use only – hands

Flammable

Keep away from fire and flame

Do not use

- on children less than 2 months of age.
- on open skin wounds.

When using this product

keep out of eyes, ears and mouth. In case of contact with eyes, rinse thoroughly with water.

Stop use and ask a doctor if

irritation or rash occurs. These may be a sign of a serious condition.

Keep out of reach of children

If swallowed, get medical help or contact a Poison Control Center right way.

Directions

Place enough product on hands to cover all surfaces. Rub hands until dry.

Supervise children under 6 years of age who are using this product to avoid swallowing.

Other Information

Store between 15 ° - 30 ° C (59° - 86°F)

Avoid freezing and excessive heat above 40°C (104°F)

Inactive Ingredients

Aloe, Fragrance, Glycerin, Hydrogen Peroxide, Reverse Osmosis Water

PRINCIPAL DISPLAY PANEL

Hand Sanitizer
Juniper scent
8 fl oz (237 ml)